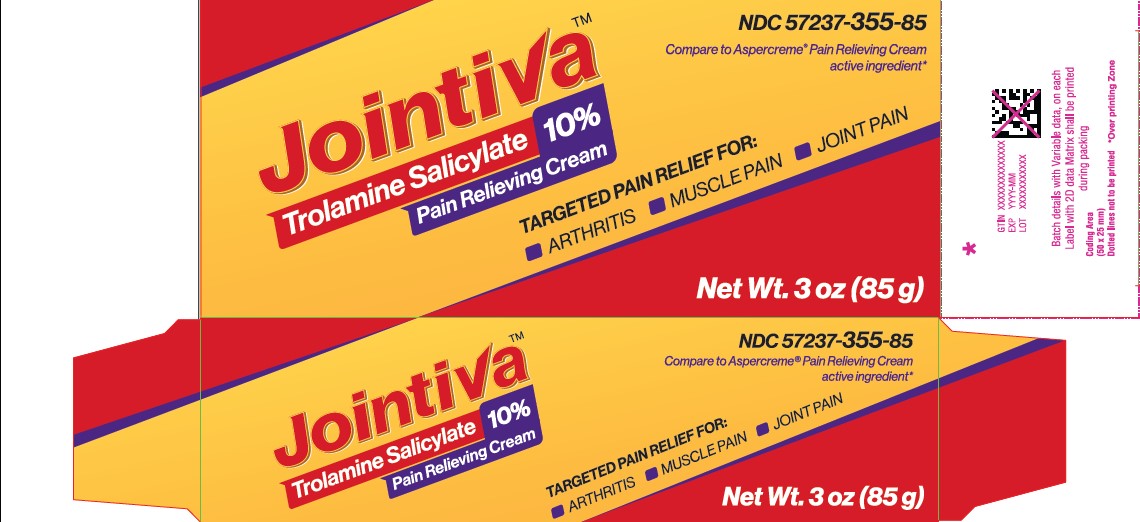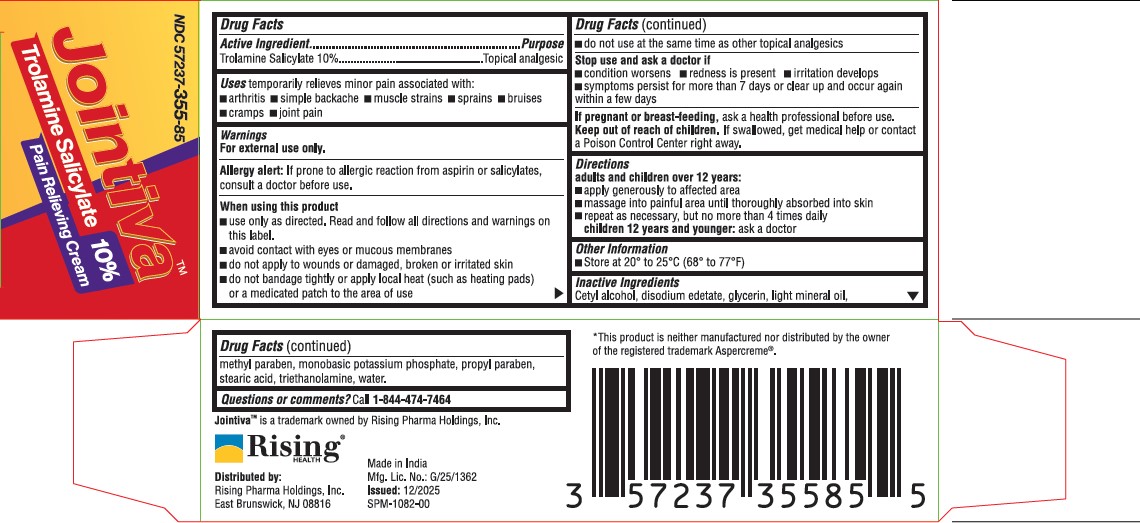 DRUG LABEL: Jointiva
NDC: 57237-355 | Form: CREAM
Manufacturer: Rising Pharma Holdings, Inc.
Category: otc | Type: HUMAN OTC DRUG LABEL
Date: 20251211

ACTIVE INGREDIENTS: TROLAMINE SALICYLATE 10 g/100 g
INACTIVE INGREDIENTS: CETYL ALCOHOL; EDETATE DISODIUM; GLYCERIN; LIGHT MINERAL OIL; METHYLPARABEN; MONOBASIC POTASSIUM PHOSPHATE; PROPYLPARABEN; STEARIC ACID; TRIETHANOLAMINE; WATER

Jointiva
Trolamine Salicylate Pain Relieving Cream

Drug Facts Active Ingredient

Trolamine Salicylate 10%

Purpose

Topical analgesic

INDICATIONS AND USAGE

Uses temporarily relieves minor pain associated with:

- arthritis
- simple backache
- muscle strains
- sprains
- bruises
- cramps
- joint pain

Warnings

For external use only.

Allergy alert: If prone to allergic reaction from aspirin or salicylates, consult a doctor before use.

When using this product

• use only as directed. Read and follow all directions and warnings on this label • avoid contact with eyes or mucous membranes • do not apply to wounds or damaged, broken or irritated skin • do not bandage tightly or apply local heat (such as heating pads) or a medicated patch to the area of use • do not use at the same time as other topical analgesics

Stop use and ask a doctor if

• condition worsens • redness is present • irritation develops • symptoms persist for more than 7 days or clear up and occur again within a few days

WHEN USING

If pregnant or breast-feeding, ask a health professional before use.

Keep out of reach of children. If swallowed, get medical help or contact a Poison Control Center right away.

Directions

adults and children over 12 years:

- apply generously to affected area
- massage into painful area until thoroughly absorbed into skin
- repeat as necessary, but no more than 4 times daily

children 12 years and younger: ask a doctor

Other Information

- Store at 20° to 25°C (68° to 77°F)

Inactive Ingredients

Cetyl alcohol, disodium edetate, glycerin, light mineral oil, methyl paraben, monobasic potassium phosphate, propyl paraben, stearic acid, triethanolamine, water.

Questions or comments?

Call 1-844-474-7464

PACKAGE LABEL

Distributed by:
Rising Pharma Holdings, Inc.
East Brunswick, NJ 08816
Made in India
Mfg. Lic. No.: G/25/1362
Issued: 12/2025